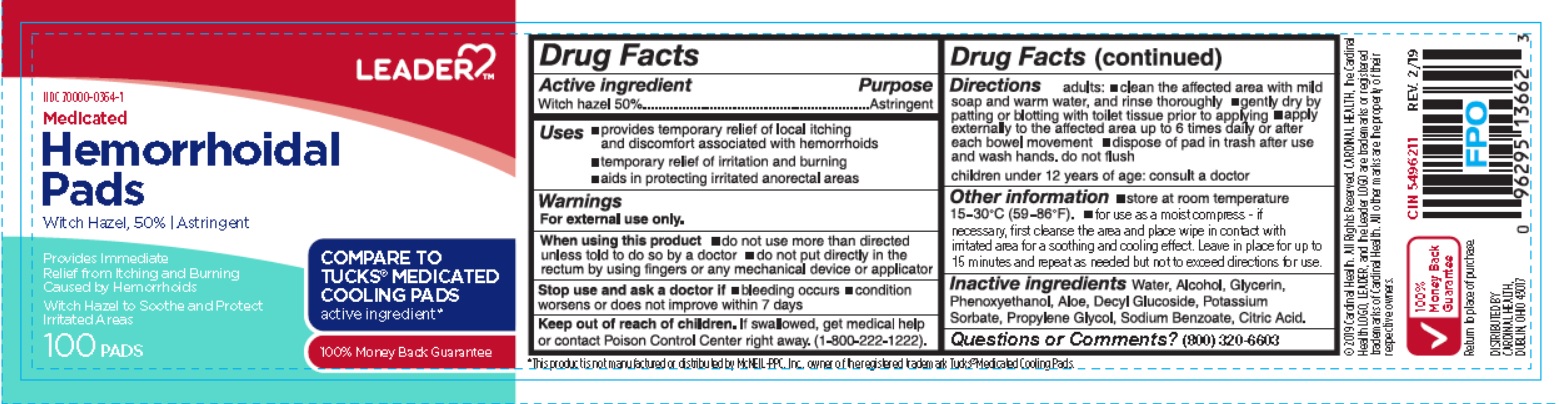 DRUG LABEL: Medicated Hemorrhoidal Pads
NDC: 70000-0364 | Form: CLOTH
Manufacturer: Cardinal Health
Category: otc | Type: HUMAN OTC DRUG LABEL
Date: 20251205

ACTIVE INGREDIENTS: WITCH HAZEL 500 mg/1 mL
INACTIVE INGREDIENTS: WATER; ALCOHOL; GLYCERIN; PHENOXYETHANOL; ALOE; DECYL GLUCOSIDE; POTASSIUM SORBATE; PROPYLENE GLYCOL; SODIUM BENZOATE; CITRIC ACID MONOHYDRATE

Drug Facts

Active ingredient

Witch hazel 50%

Purpose

Astringent

Uses

- provides temporary relief of local itching and discomfort associated with hemorrhoids
- temporary relief of irritation and burning.
- aids in protecting irritated anorectal areas.

Warnings

For external use only.

When using this product

- do not use more than directed unless told to do so by a doctor
- do not put directly in the rectum by using fingers or any mechanical device or applicator.

Stop use and ask a doctor if

- bleeding occurs
- condition worsens or does not improve within 7 days

Keep out of reach of children.

If swallowed, get medical help or contact Poison Control Center right away. (1-800-222-1222).

Directions

adults:

- cleane the affected area with mild soap and warm water, and rinse thoroughly
- gently dry by patting or blotting with toilet tissue prior to applying.
- apply externally to the affected area up to 6 times daily or after each bowel movement
- dispose of pad in thrash after use and wash hands, do not flush

children under 12 years of age: consult a doctor

Other Information

- store at room temperature 15- 30oC (59 - 86oF)
- for use as a moist compress - if necessary, ﬁrst cleanse the area and place wipe in contact with irritated area for a soothing and cooling effect. Leave in place for up to 15 minutes and repeat as needed but not to exceed directions for use.

Inactive ingredients

Water, Alcohol, Glycerin, Phenoxyethanol, Aloe, Decyl Glucoside, Potassium Sorbate, Propylene Glycol, Sodium Benzoate, Citric Acid.

Questions or Comments?

(800) 320-6603

Principal Display Panel

LEADERTM

NDC 70000-0364-1

Medicated Hemorrhoidal Pads

WITCH HAZEL, 50% | Astringent

Provides Immediate Relief from Itching and Burning Caused by Hemorrhoids

Witch Hazel to Soothe and Protect Irritated Areas

COMPARE TO TUCKS® MEDICATED COOLING PADS active ingredient*

100% Money Back Guarantee

100 PADS

*This product is not manufactured or distributed by McNEIL-PPC, Inc., owner of the registered trademark Tucks® Medicated Cooling Pads.